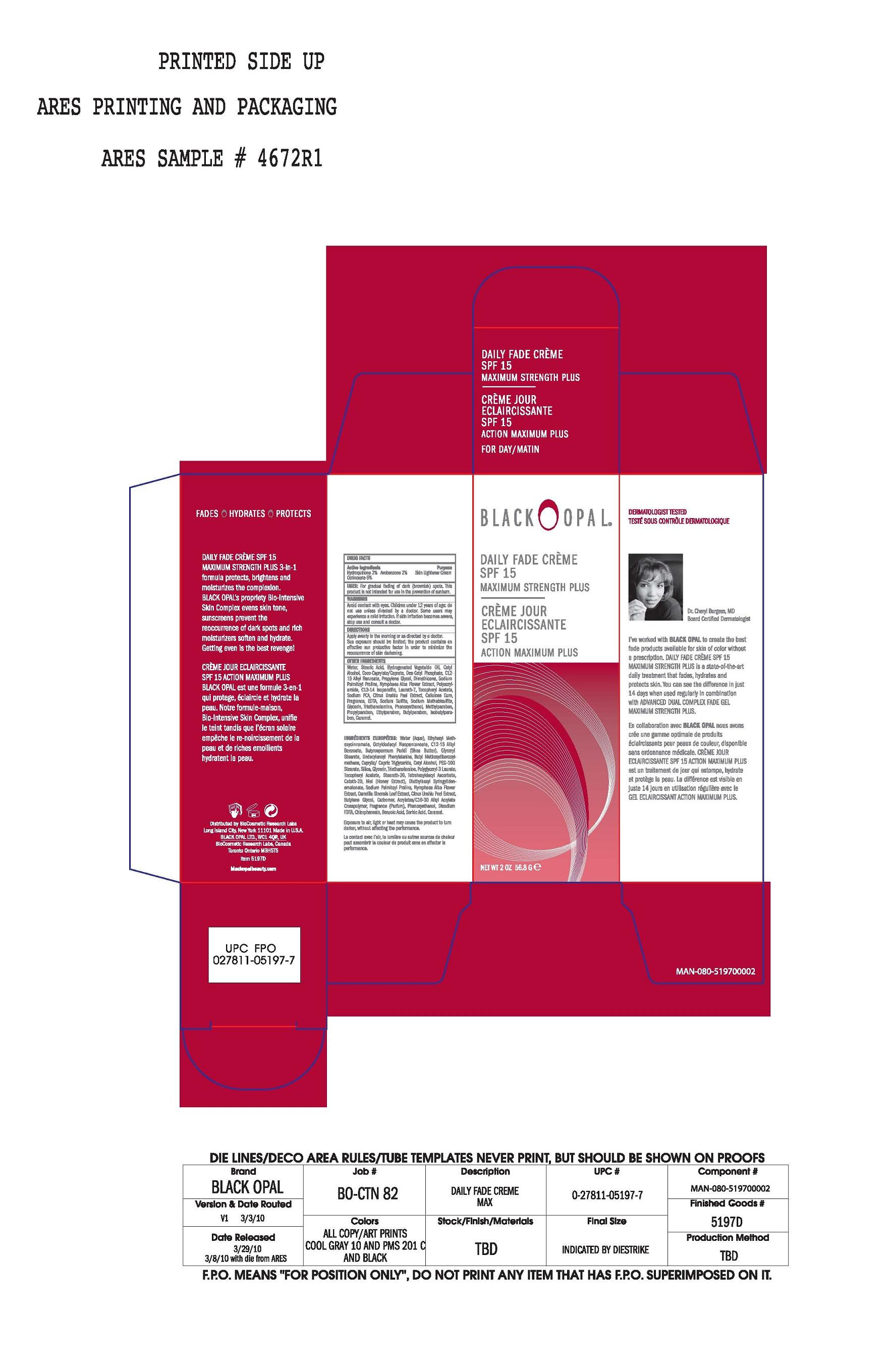 DRUG LABEL: Daily Fade 
NDC: 59735-308 | Form: CREAM
Manufacturer: Biocosmetic Research Labs
Category: otc | Type: HUMAN OTC DRUG LABEL
Date: 20090603

ACTIVE INGREDIENTS: Hydroquinone  2 g/100 g; Avobenzone 2 g/100 g; Octinoxate 5 g/100 g

Daily Fade Creme SPF 15 Maximum Strength

Active Ingredients:

Hydroquinone 2%

Avobenzone 2%

Octinoxate 5%

Purpose:

Skin Lightener Cream

Uses:

For gradual fading of dark (brownish) spots. This product is not intended for use in the prevention of sunburn.

Warnings:

Avoid Contact with eyes. Children under 12 years of age; Do not use unless directed by a doctor.

STOP USE

Some users may experience a mild irritation. If skin irritation becomes severe, stop use and consult a doctor.

Directions:

Apply evenly in the morning or as directed by a doctor. Sun exposure should be limited; the product contains an effective sun protection factor in order to minimize the reoccurrence of skin darking.

INACTIVE INGREDIENT

Other Ingredients:

Water, Stearic Acid, Hydrogenated Vegetable Oil, Cetyl Alcohol, Coco-Caprylate/Caprate, DEA-Cetyl Phosphate, C12-15 Alkyl Benzoate, Propylene Glycol, Dimethicone, Sodium Palmitoyl Proline, Nymphaea Alba Flower Extract, Polyacrylamide, C13-14 Isoparaffin, Lureth-7, Tocopheryl Acetate, Sodium PCA, Citrus Unshiu Peel Extract, Cellulose Gum, Fragrance, EDTA, Sodium Sulfite, Sodium Methabisulfite, Glycerin, Triethanolamine, Phenoxyethanol, Methylparaben, Propylparaben, Ethylparaben, Butylparaben, Isobutylparaben, Caramel.